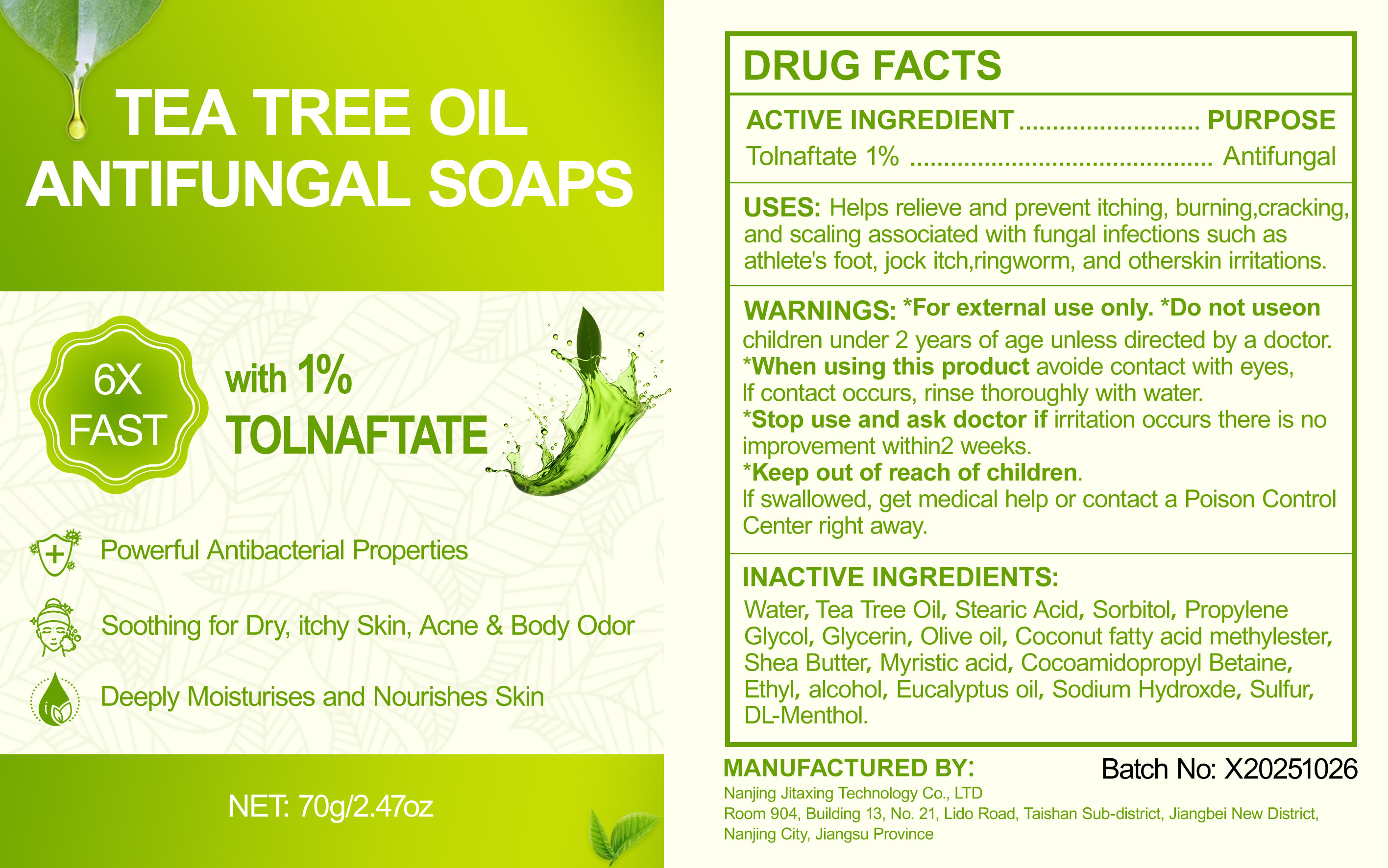 DRUG LABEL: Tea Tree Oil Antifungal Soaps
NDC: 87257-001 | Form: SOAP
Manufacturer: Nanjing Jitaxing Technology Co., LTD
Category: otc | Type: HUMAN OTC DRUG LABEL
Date: 20251203

ACTIVE INGREDIENTS: TOLNAFTATE 0.7 g/70 g
INACTIVE INGREDIENTS: PROPYLENE GLYCOL; SHEA BUTTER; MYRISTIC ACID; STEARIC ACID; GLYCERIN; OLIVE OIL; ETHYL-DDD; TEA TREE OIL; EUCALYPTUS OIL; SODIUM HYDROXIDE; RACEMENTHOL; WATER; SULFUR; SORBITOL; METHYL COCOATE; COCAMIDOPROPYL BETAINE; ALCOHOL

87257-001 Tea Tree Oil Antifungal Soap

ACTIVE INGREDIENT

Tolnaftate 1%

PURPOSE

Antifungal

INDICATIONS AND USAGE

USES: Helps relieve and prevent itching, burning,crackingand scaling associated with fungal infections such asathlete's foot, jock itch,ringworm, and otherskin irritations

WARNINGS

For external use only

DO NOT USE

Do not useon children under 2 years of age unless directed by a doctor.

When using this product avoide contact with eyes If contact occurs, rinse thoroughly with water.

Stop use and ask doctor if irritation occurs there is no improvement within2 weeks.

KEEP OUT OF REACH OF CHILDREN

If swallowed, get medical help or contact a Poison Control
Center right away.

DOSAGE AND ADMINISTRATION

Powerful Antibacterial Properties Soothing for Dry, itchy Skin, Acne & Body Odor Deeply Moisturises and Nourishes Skin

INACTIVE INGREDIENT

Water, Tea Tree Oil, Stearic Acid, Sorbitol, Propylene Glycol, Glycerin, Olive oil, Coconut fatty acid methylester, Shea Butter, Myristic acid, Cocoamidopropyl Betaine, Ethyl, alcohol, Eucalyptus oil, Sodium Hydroxde, Sulfur, DL-Menthol.